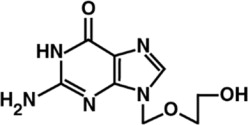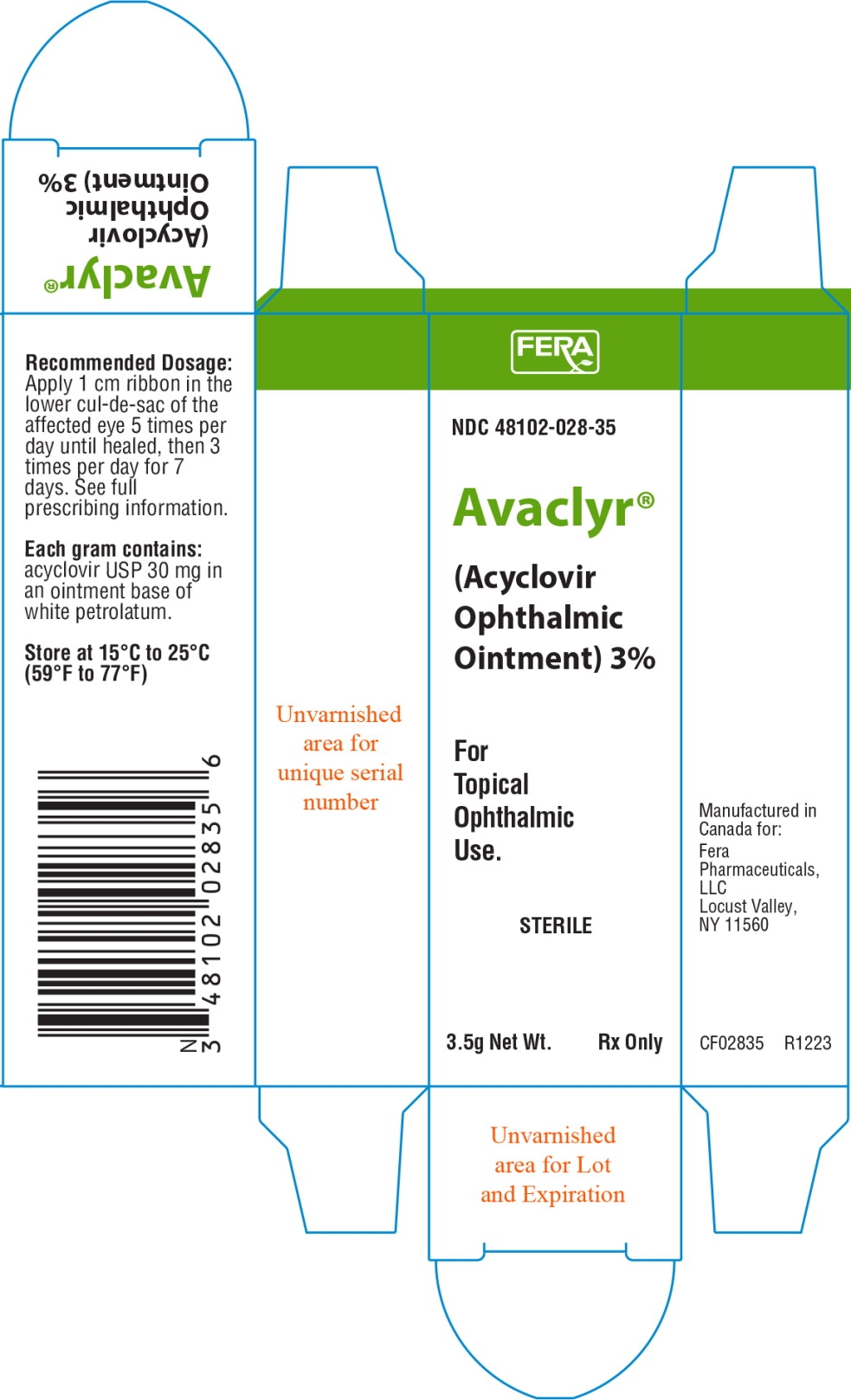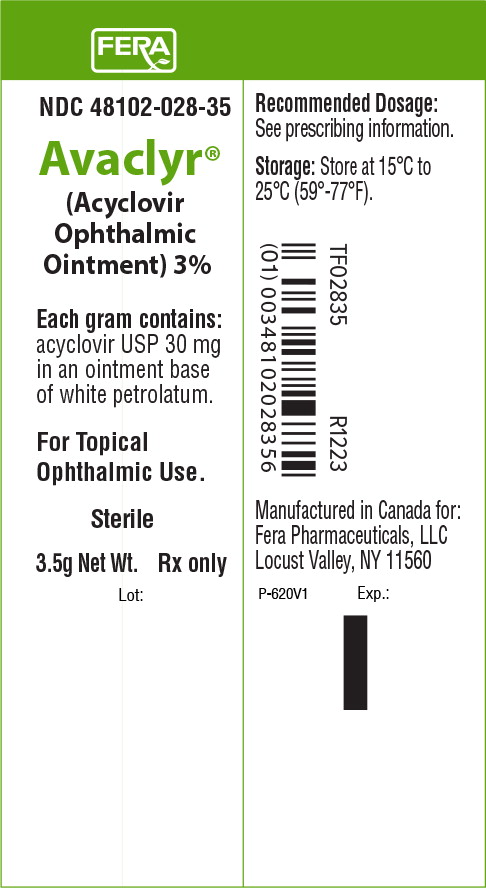 DRUG LABEL: Avaclyr
NDC: 48102-028 | Form: OINTMENT
Manufacturer: Fera Pharmaceuticals, LLC
Category: prescription | Type: HUMAN PRESCRIPTION DRUG LABEL
Date: 20260105

ACTIVE INGREDIENTS: ACYCLOVIR 30 mg/1 g
INACTIVE INGREDIENTS: WHITE PETROLATUM

HIGHLIGHTS OF PRESCRIBING INFORMATION

These highlights do not include all the information needed to use AVACLYR safely and effectively. See full prescribing information for AVACLYR.
AVACLYR® (acyclovir ophthalmic ointment) 3%, for topical ophthalmic use
Initial U.S. Approval: 1982

1 INDICATIONS AND USAGE

AVACLYR (acyclovir ophthalmic ointment) 3%, a herpes simplex virus nucleoside analog DNA polymerase inhibitor, is indicated in the treatment of acute herpetic keratitis (dendritic ulcers) in patients with herpes simplex (HSV-1 and HSV-2) virus.

2 DOSAGE AND ADMINISTRATION

Apply a 1 cm ribbon in the lower cul-de-sac of the affected eye 5 times per day until healed then 3 times per day for 7 days. (2)

3 DOSAGE FORMS AND STRENGTHS

Ophthalmic ointment containing 3% acyclovir.

4 CONTRAINDICATIONS

AVACLYR is contraindicated in patients with a known hypersensitivity to acyclovir or valacyclovir.

5 WARNINGS AND PRECAUTIONS

- AVACLYR is indicated for topical ophthalmic use. (5.1)
- Patients should not wear contact lenses if they have signs or symptoms of herpetic keratitis or during the course of therapy with AVACLYR. (5.2)

6 ADVERSE REACTIONS

The most common adverse reactions (2 to 10%) reported in patients were eye pain (stinging), punctate keratitis and follicular conjunctivitis. (6)

To report SUSPECTED ADVERSE REACTIONS, contact Fera Pharmaceuticals, LLC at (414) 434-6604 or FDA at 1-800-FDA-1088 or www.fda.gov/medwatch.

FULL PRESCRIBING INFORMATION

1 INDICATIONS AND USAGE

AVACLYR is a sterile topical antiviral indicated for the treatment of acute herpetic keratitis (dendritic ulcers) in patients with herpes simplex (HSV-1 and HSV-2) virus.

2 DOSAGE AND ADMINISTRATION

The recommended dosing regimen is to apply a 1 cm ribbon of ointment in the lower cul-de-sac of the affected eye 5 times per day (approximately every 3 hours while awake) until the corneal ulcer heals and then a 1 cm ribbon 3 times per day for 7 days.

3 DOSAGE FORMS AND STRENGTHS

AVACLYR is an ophthalmic ointment containing 3% acyclovir.

4 CONTRAINDICATIONS

AVACLYR is contraindicated for patients who develop sensitivity to acyclovir or valacyclovir.

5 WARNINGS AND PRECAUTIONS

5.1 Topical Ophthalmic Use

AVACLYR is indicated for topical ophthalmic use.

5.2 Avoidance of Contact Lenses

Patients should not wear contact lenses if they have signs or symptoms of herpetic keratitis or during the course of therapy with AVACLYR.

5.3 Risk of Contamination

This product is sterile when packaged. Patients should be advised to not allow the tip of the container to touch any surface, as this may contaminate the ointment. If pain develops, or if redness, itching, or inflammation becomes aggravated, the patient should be advised to consult a physician.

6 ADVERSE REACTIONS

The most common adverse reactions (2-10%) reported in patients were eye pain (stinging), punctate keratitis and follicular conjunctivitis. Rare reports of blepharitis and very rare reports of immediate hypersensitivity reactions including angioedema and urticaria have been observed post-marketing in patients taking AVACLYR.

7 DRUG INTERACTIONS

No clinically significant interactions have been identified resulting from topical administration of other drugs concomitantly with AVACLYR.

8 USE IN SPECIFIC POPULATIONS

8.1 Pregnancy

Risk Summary

A prospective epidemiologic registry of acyclovir use from 1984 to 1999 indicated that the occurrence rate of birth defects in women exposed to systemically administered acyclovir during the first trimester of pregnancy (period of organogenesis) approximated that found in the general population. Likewise, oral and subcutaneous administration of acyclovir to pregnant mice, rats, and rabbits during organogenesis did not produce teratogenicity at clinically relevant doses (see Animal Data).

Data

Human Data

A prospective epidemiologic registry of acyclovir use during pregnancy was established in 1984 and completed in April 1999. There were 749 pregnancies followed in women exposed to systemically administered acyclovir during the first trimester of pregnancy resulting in 756 outcomes. The occurrence rate of birth defects approximates that found in the general population. However, the small size of the registry is insufficient to evaluate the risk for less common defects, or to permit reliable or definitive conclusions regarding the safety of acyclovir in pregnant women and their developing fetuses. The human maternal plasma level of acyclovir following ocular administration is unknown.

Animal Data

In published animal reproduction studies, acyclovir was not maternally toxic and did not produce teratogenicity in the mouse at oral doses up to 450 mg/kg/day (1100 times the maximum recommended human ophthalmic dose [RHOD] on a mg/m^2 basis, assuming 100% absorption), or in the rat and rabbit at subcutaneous doses up to 50 mg/kg/day (approximately 250 and 500 times the RHOD, respectively) when administered throughout the period of organogenesis.

Administration of acyclovir from postnatal days 3 to 21 did not produce adverse effects in neonatal rats at subcutaneous doses less than or equal to 20 mg/kg/day (100 times the RHOD).

8.2 Lactation

Risk Summary

Acyclovir concentrations have been documented in breast milk following oral administration of acyclovir. There is no information regarding the presence of acyclovir in human milk following ocular administration, the effects on the breastfed infant, or the effects on milk production. The developmental and health benefits of breastfeeding should be considered along with the mother's clinical need for acyclovir, and any potential adverse effects on the breast-fed child from acyclovir or from the underlying maternal condition.

8.4 Pediatric Use

Safety and efficacy of Acyclovir ophthalmic ointment in pediatric patients below the age of two years has not been established.

8.5 Geriatric Use

No overall differences in safety or effectiveness have been observed between elderly and other adult patients.

10 OVERDOSAGE

Overdosage of topical application of acyclovir 3% is unlikely because of minimal absorption.

11 DESCRIPTION

Acyclovir is a synthetic herpes simplex virus nucleoside analog DNA polymerase inhibitor. The drug substance is a white crystalline powder with the molecular formula of C8H11N5O3 and a molecular weight of 225.2. The maximum solubility in water at 25°C is 1.41 mg/mL. The pka's of acyclovir are 2.52 and 9.35.

The chemical name of acyclovir is 2-amino-1,9-dihydro-9-[(2-hydroxyethoxy)methyl]6H-purin-6-one, it has the following chemical structure:

AVACLYR is a sterile ointment for topical administration in eyes. Each gram of ointment contains 30 mg of acyclovir in a white petrolatum base.

12 CLINICAL PHARMACOLOGY

12.1 Mechanism of Action

Acyclovir is an antiviral drug [see Microbiology (12.4)].

12.3 Pharmacokinetics

It has not been possible to detect acyclovir concentrations in the blood by existing bioanalytical methods after topical application to the eye. Trace quantities are detectable in the urine but are not therapeutically relevant.

12.4 Microbiology

Acyclovir is a synthetic purine nucleoside analogue that is phosphorylated intracellularly by the viral encoded thymidine kinase (TK) of HSV into acyclovir monophosphate, a nucleotide analogue. The monophosphate is further converted into diphosphate by cellular guanylate kinase and into triphosphate by a number of cellular enzymes. In a biochemical reaction, acyclovir triphosphate inhibits replication of herpes viral DNA by competing with nucleotides for binding to the viral DNA polymerase and by incorporation into and termination of the growing viral DNA chain. The cellular thymidine kinase of normal, uninfected cells does not use acyclovir effectively as a substrate, hence toxicity to mammalian host cells is low.

Antiviral Activities: The quantitative relationship between the cell culture susceptibility of herpes virus to antivirals and the clinical response to therapy has not been established in humans, and virus sensitivity testing has not been standardized. Sensitivity testing results, expressed as the concentration of drug required to inhibit by 50% the growth of virus in cell culture (EC50), vary greatly depending upon a number of factors. Using plaque-reduction assays, on Vero cells, the median EC50 value of acyclovir against clinical herpes simplex virus isolates (subjects receiving placebo) was 1.3 μM (range: < 0.56 to 3.3 μM).

Drug Resistance: Resistance of HSV to acyclovir can result from qualitative and quantitative changes in the viral TK and/or DNA polymerase. Clinical isolates of HSV with reduced susceptibility to acyclovir have been recovered from immunocompromised patients, especially with advanced HIV infection. While most of the acyclovir resistant mutant isolates thus far from such patients have been found to be TK deficient, other mutant isolates involving the viral TK gene (TK partial and TK altered) or DNA polymerase have been identified. TK negative mutants may cause severe disease in infants and immunocompromised adults. The possibility of viral resistance to acyclovir should be considered in immunocompromised patients who show poor clinical response during therapy.

13 NON-CLINICAL TOXICOLOGY

13.1 Carcinogenesis, Mutagenesis, Impairment of Fertility

Carcinogenesis

Acyclovir was not shown to be carcinogenic in mouse and rat bioassays at oral doses up to 450 mg/kg (approximately 1100 – 2200 times the maximum RHOD, on a mg/m^2 basis, assuming 100% absorption).

Mutagenesis

Acyclovir was tested in 16 in vitro and in vivo genetic toxicity assays. Acyclovir was found to be negative in the Ames test, positive in the in vitro mouse lymphoma assay (TK locus), and positive in the in vitro and in vivo assays for chromosomal effects.

Impairment of Fertility

In reproduction studies, acyclovir did not impair fertility or reproduction at oral doses up to 450 mg/kg/day in mice (1100 times the RHOD), or at subcutaneous doses of 25 mg/kg/day in rats (125 times the RHOD). At a dose of 50 mg/kg/day in rats and rabbits (250 and 500 times the RHOD, respectively), implantation efficiency was decreased.

14 CLINICAL STUDIES

In five randomized, double masked studies which enrolled a total of 238 subjects with dendritic herpetic keratitis, acyclovir ophthalmic ointment, 3% was either superior or as effective as idoxuridine ophthalmic ointment 0.5% or 1% in subjects with dendritic ulcers. Clinical resolution (healed ulcers) at Day 7 averaged 83% for acyclovir and 50% for idoxuridine.

16 HOW SUPPLIED/STORAGE AND HANDLING

AVACLYR is available in a 3.5 g aluminum tube with a white high density polyethylene cap as a clear, colorless, sterile ophthalmic ointment for topical use containing 3% acyclovir active drug. Each tube is packaged in an individual carton.

3.5 g tube (NDC 48102-028-35)

Store at 15°C to 25°C (59°F to 77°F).

17 PATIENT COUNSELING INFORMATION

Administration

Advise patients to wash hands well and pull down lower lid of the affected eye to form a pocket. Instruct the patient to apply a 1 cm (1/2 inch) ribbon of ointment in the pocket formed by the lower lid 5 times per day (approximately every 3 hours while awake). After application of the ointment, the patient should be advised to close their eye for 1-2 minutes. Excess ointment can be wiped away. Continue this dosing 5 times per day until the patient is advised by their physician that the corneal ulcer is healed. Once healed, instruct the patient to continue use of a 1 cm (1/2 inch) ribbon of ointment 3 times per day for 7 more days. [see Dosage and Administration (2)].

Risk of Contamination

This product is sterile when packaged. Advise patients to not allow the tip of the container to touch any surface, as this may contaminate the ointment.

When to Consult a Physician

Advise patients to consult a physician if pain develops, or if redness, itching, or inflammation becomes aggravated.

Avoidance of Contact Lenses

Advise patients to not wear contact lenses when using AVACLYR.

Manufactured in Canada for:

Fera Pharmaceuticals, LLC

Locust Valley, N.Y. 11560

PF028 P-622V1

Principal Display Panel - 30 mg Carton Label

FERA

NDC 48102-028-35

Avaclyr®

(Acyclovir
Ophthalmic
Ointment) 3%

For
Topical
Ophthalmic
Use.

STERILE

3.5g Net Wt. Rx only

Principal Display Panel - 30 mg Tube Label

FERA

NDC 48102-028-35

Avaclyr®

(Acyclovir
Ophthalmic
Ointment) 3%

Each gram contains:

acyclovir USP 30 mg
in an ointment base
of white petrolatum.

For Topical
Ophthalmic Use.

Sterile

3.5g Net Wt. Rx only

Lot: